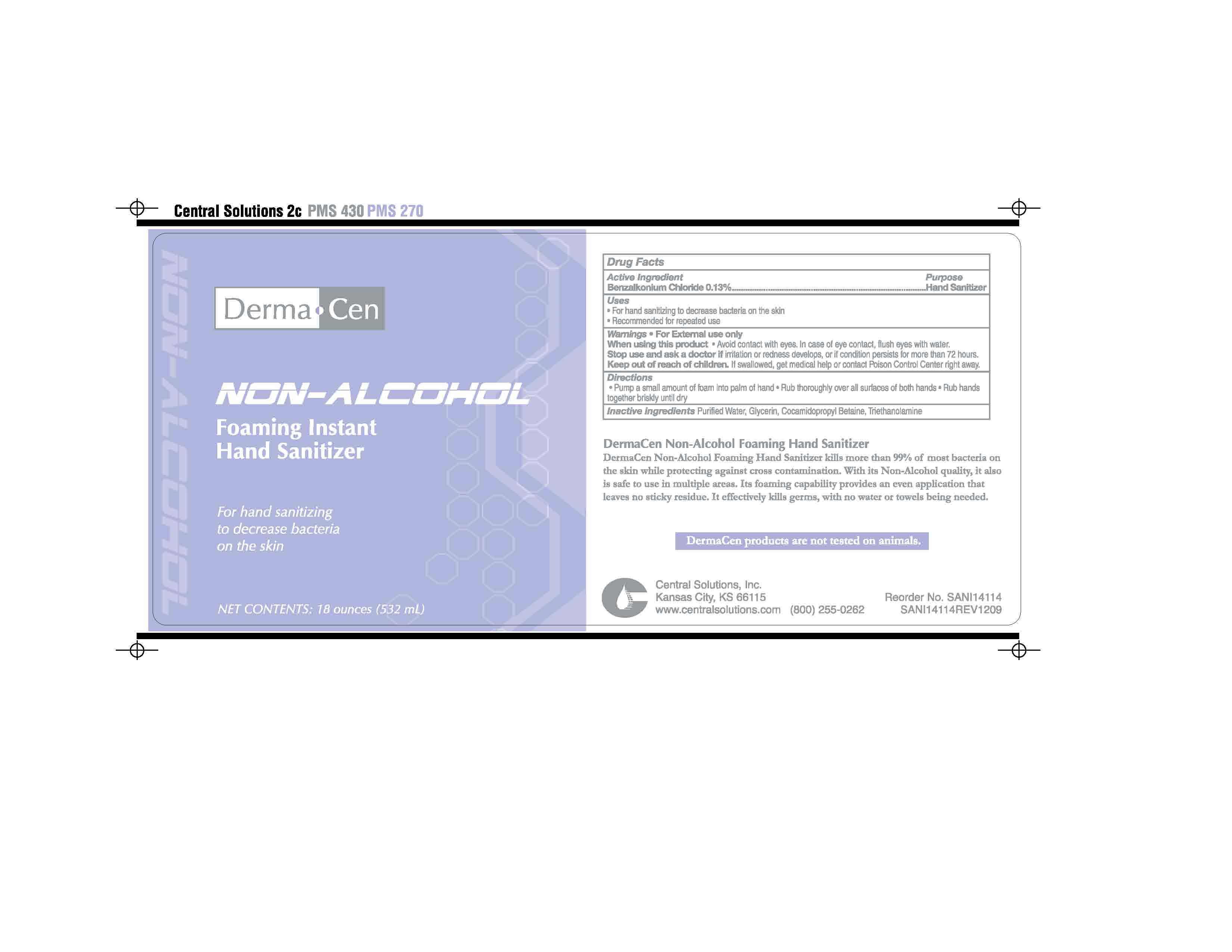 DRUG LABEL: DermaCen Non-Alcohol Foaming Hand Sanitizer
NDC: 62654-141 | Form: SOLUTION
Manufacturer: Central Solutions Inc
Category: otc | Type: HUMAN OTC DRUG LABEL
Date: 20241209

ACTIVE INGREDIENTS: BENZALKONIUM CHLORIDE 0.13 g/100 mL
INACTIVE INGREDIENTS: WATER; GLYCERIN; COCAMIDOPROPYL BETAINE

Drug Facts 62654-141

Active ingredient

Benzalkonium Chloride 0.13%

Uses

For hand sanitizing to decrease bacteria on the skin

Recommended for repeated use

Warnings

For external use only

When using this product avoid contact with eyes.

In case of eye contact, flush with water.

Stop use and ask a doctor if irritation or redness develops, or if conditions persists for more than 72 hours.

Keep out of reach of children. If swallowed, call a physician or Poison Control Center right away.

Directions

Pump a small amount of foam into palm of hand

Rub thoroughly over all surfaces of both hands

Rub hands together briskly until dry

Inactive ingredients

Purified Water, Glycerin, Cocamidopropyl Betaine, Triethanolamine

Purpose

Hand Sanitizer

PACKAGE LABEL

DermaCen

Non-Alcohol

Foaming Instant

Hand Sanitizer

For hand sanitizing

to decrease bacteria

on the skin

NET CONTENTS: 18 ounces (532 mL)